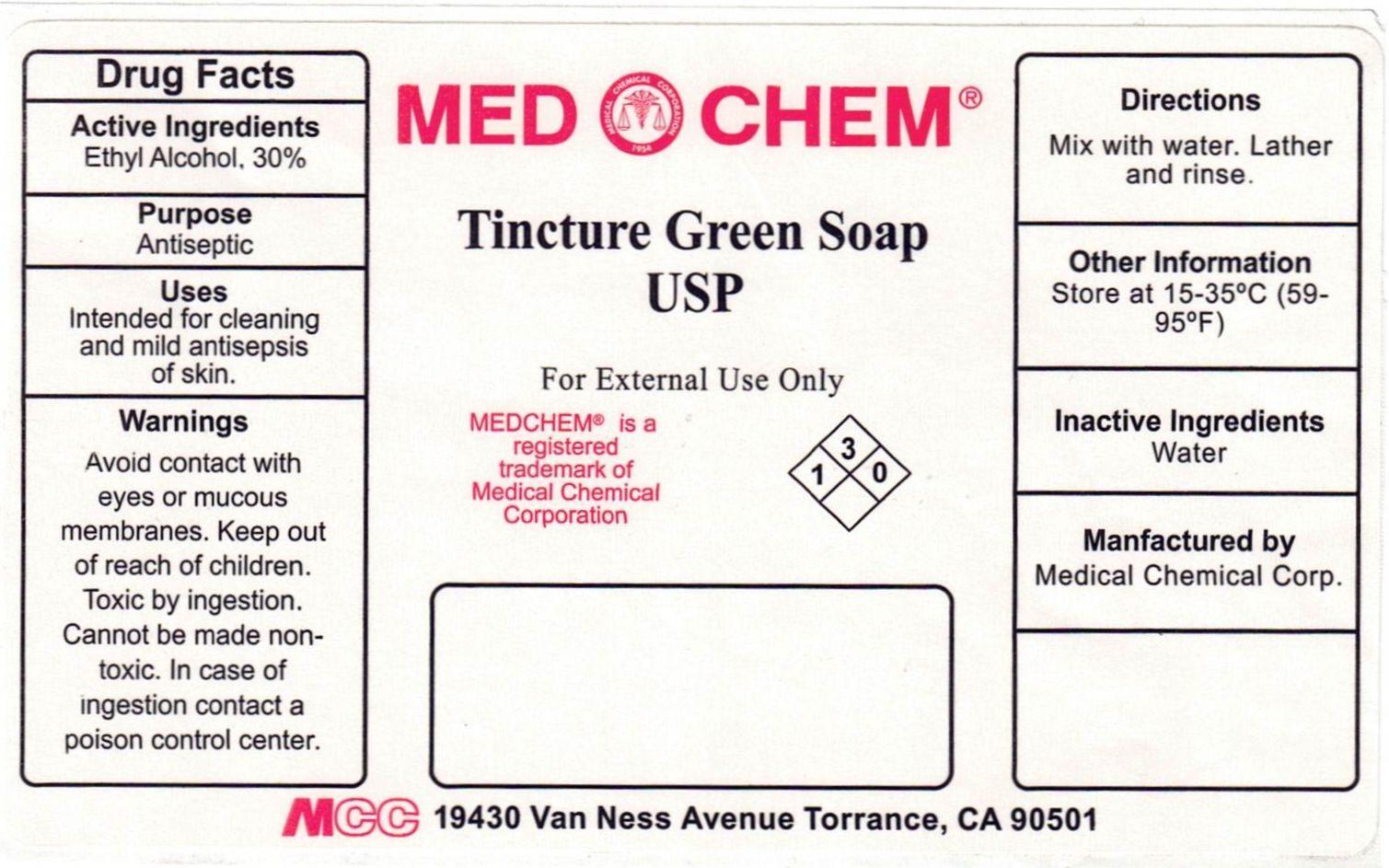 DRUG LABEL: Tincture Green
NDC: 12745-041 | Form: LIQUID
Manufacturer: Medical Chemical Corporation
Category: otc | Type: HUMAN OTC DRUG LABEL
Date: 20220117

ACTIVE INGREDIENTS: ALCOHOL 30 mL/100 mL
INACTIVE INGREDIENTS: LAVENDER OIL 0.225 g/100 mL; OLEIC ACID 1.3 g/100 mL; TALL OIL 24.7 g/100 mL; POTASSIUM HYDROXIDE 10.13 g/100 mL; GLYCERIN 4.052 g/100 mL; WATER 30.08 mL/100 mL

TINCTURE GREEN SOAP

ACTIVE INGREDIENT

Ethyl Alcohol, 30%

KEEP OUT OF REACH OF CHILDREN

Warnings: Avoid contact with eyes or mucous membranes. Keep out of reach of children. Toxic by ingestion. Cannot be made nontoxic. In case of ingestion contact a poison control center.

INDICATIONS AND USAGE

Uses: Intended for cleaning and mild antisepsis of skin.

WARNINGS

Warnings: Avoid contact with eyes or mucous membranes. Keep out of reach of children. Toxic by ingestion. Cannot be made nontoxic. In case of ingestion contact a poison control center.

DOSAGE AND ADMINISTRATION

Directions: Mix with water. Lather and rinse.

Inactive Ingredients: Water

Purpose: Antiseptic